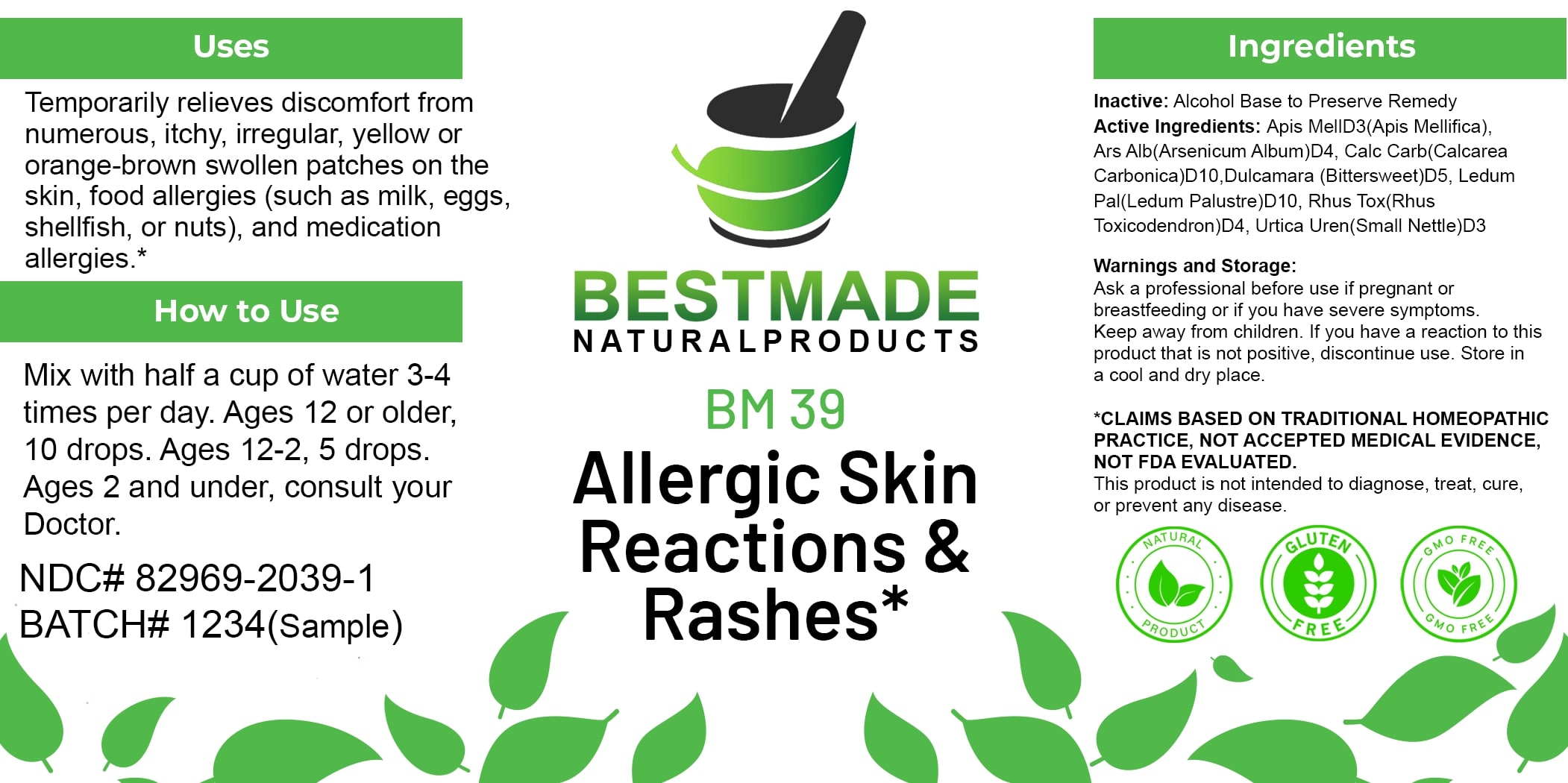 DRUG LABEL: Bestmade Natural Products BM39
NDC: 82969-2039 | Form: LIQUID
Manufacturer: Bestmade Natural Products
Category: homeopathic | Type: HUMAN OTC DRUG LABEL
Date: 20250123

ACTIVE INGREDIENTS: ARSENIC TRIOXIDE 30 [hp_C]/30 [hp_C]; OYSTER SHELL CALCIUM CARBONATE, CRUDE 30 [hp_C]/30 [hp_C]; SOLANUM DULCAMARA TOP 30 [hp_C]/30 [hp_C]; URTICA URENS 30 [hp_C]/30 [hp_C]; LEDUM PALUSTRE WHOLE 30 [hp_C]/30 [hp_C]; TOXICODENDRON PUBESCENS LEAF 30 [hp_C]/30 [hp_C]; APIS MELLIFERA 30 [hp_C]/30 [hp_C]
INACTIVE INGREDIENTS: ALCOHOL 30 [hp_C]/30 [hp_C]

BM39

DOSAGE AND ADMINISTRATION

How to Use

Mix with half a cup of water 3-4 times per day. Ages 12 or older, 10 drops. Ages 12-2, 5 drops. Ages 2 and under, consult your Doctor.

INACTIVE INGREDIENT

Ingredients

Inactive: Alcohol Base to Preserve Remedy

Uses

Temporarily relieves discomfort from numerous, itchy, irregular, yellow or orange-brown swollen patches on the skin, food allergies (such as milk, eggs, shellfish, or nuts), and medication allergies.*

*CLAIMS BASED ON TRADITIONAL HOMEOPATHIC PRACTICE, NOT ACCEPTED MEDICAL EVIDENCE, NOT FDA EVALUATED.

This product is not intended to diagnose, treat, cure, or prevent any disease.

Uses

Temporarily relieves discomfort from numerous, itchy, irregular, yellow or orange-brown swollen patches on the skin, food allergies (such as milk, eggs, shellfish, or nuts), and medication allergies.*

*CLAIMS BASED ON TRADITIONAL HOMEOPATHIC PRACTICE, NOT ACCEPTED MEDICAL EVIDENCE, NOT FDA EVALUATED.

This product is not intended to diagnose, treat, cure, or prevent any disease.

ACTIVE INGREDIENT

Active Ingredients: Apis Mell D3 (Apis Mellifica), Ars Alb (Arsenicum Album) D4, Calc Carb (Calcarea Carbonica) D10, Dulcamara (Bittersweet) D5, Ledum Pal (Ledum Palustre) D10, Rhus Tox (Rhus Toxicodendron) D4, Urtica Uren (Small Nettle) D3

KEEP OUT OF REACH OF CHILDREN

Warnings and Storage:

Ask a professional before use if pregnant or breastfeeding or if you have severe symptoms. Keep away from children. If you have a reaction to this product that is not positive, discontinue use. Store in a cool and dry place.

Warnings and Storage:

Ask a professional before use if pregnant or breastfeeding or if you have severe symptoms. Keep away from children. If you have a reaction to this product that is not positive, discontinue use. Store in a cool and dry place.

*CLAIMS BASED ON TRADITIONAL HOMEOPATHIC PRACTICE, NOT ACCEPTED MEDICAL EVIDENCE, NOT FDA EVALUATED.

This product is not intended to diagnose, treat, cure, or prevent any disease.

Entire package label